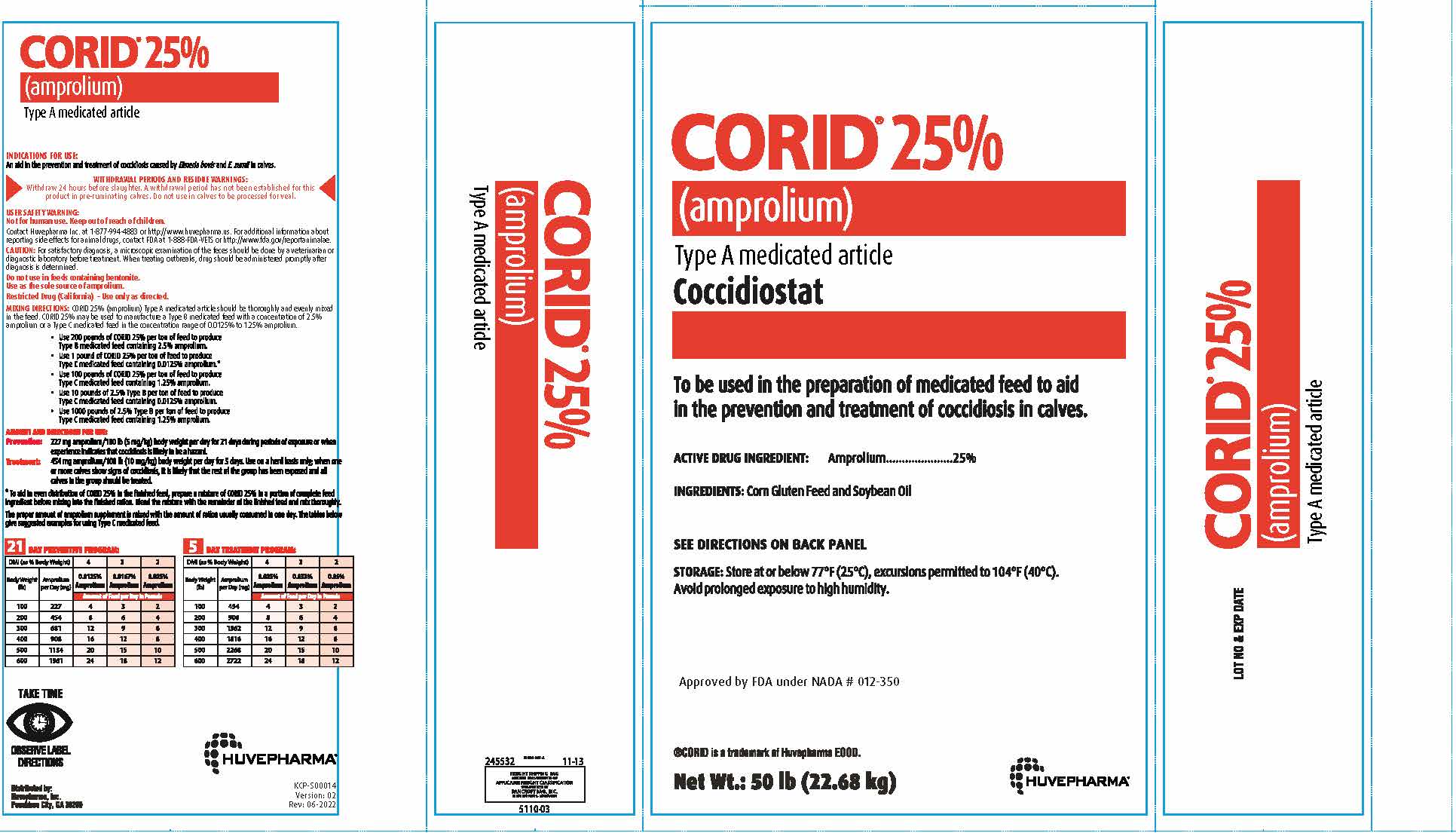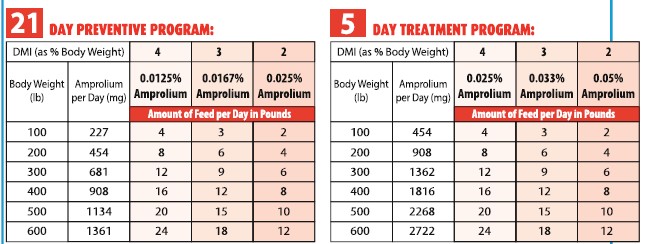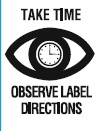 DRUG LABEL: CORID
NDC: 23243-9704 | Form: granule
Manufacturer: Huvepharma, Inc.
Category: animal | Type: OTC TYPE A MEDICATED ARTICLE ANIMAL DRUG LABEL
Date: 20251013

ACTIVE INGREDIENTS: amprolium 250 mg/0.001 kg
INACTIVE INGREDIENTS: AMINO ACIDS, CORN GLUTEN; SOYBEAN OIL

CORID® 25%
(amprolium)
Type A Medicated Article
Coccidiostat

VETERINARY INDICATIONS

To be used in the preparation of medicated feed to aid
in the prevention and treatment of coccidiosis in calves.

ACTIVE DRUG INGREDIENT: Amprolium ..................... 25%

INACTIVE INGREDIENT

INGREDIENTS: Corn Gluten Feed and Soybean Oil

STORAGE AND HANDLING

SEE DIRECTIONS ON BACK PANEL

STORAGE: Store at or below 77°F (25°C), excursions permitted to 104°F (40°C).
Avoid prolonged exposure to high humidity.

Approved by FDA under NADA # 012-350

®CORID is a trademark ot Huvepharma EOOD.
Net Wt.: 50 lb (22.68 kg)

CORID® 25%
(amprolium)
Type A Medicated Article

INDICATIONS FOR USE:
An aid in the prevention and treatment of coccidiosis caused by Eimeria bovis and E. zurnii in calves.

WITHDRAWAL PERIODS AND RESIDUE WARNINGS:
Withdraw 24 hours before slaughter. A withdrawal period has not been established for this
product in pre-ruminating calves. Do not use in calves to be processed for veal.

USER SAFETY WARNING:
Not for human use. Keep out of reach of children.
Contact Huvepharma Inc. at 1-877-994-4883 or http://www.huvepharma.us. For additional information about
reporting side effects for animal drugs, contact FDA at 1-888-FDA-VETS or http://www.fda.gov/reportanimalae.

PRECAUTIONS

CAUTION: For satisfactory diagnosis, a microscopic examination of the feces should be done by a veterinarian or
diagnostic laboratory before treatment. When treating outbreaks, drug should be administered promptly after
diagnosis is determined.

Do not use in feeds containing bentonite.
Use as the sole source of amprolium.
Restricted Drug (California) – Use only as directed.

DOSAGE AND ADMINISTRATION

MIXING DIRECTIONS: CORID 25% (amprolium) Type A medicated article should be thoroughly and evenly mixed
in the feed. CORID 25% may be used to manufacture a Type B medicated feed with a concentration of 2.5%
amprolium or a Type C medicated feed in the concentration range of 0.0125% to 1.25% amprolium.
• Use 200 pounds of CORID 25% per ton of feed to produce
Type B medicated feed containing 2.5% amprolium.
• Use 1 pound of CORID 25% per ton of feed to produce
Type C medicated feed containing 0.0125% amprolium.*
• Use 100 pounds of CORID 25% per ton of feed to produce
Type C medicated feed containing 1.25% amprolium.
• Use 10 pounds of 2.5% Type B per ton of feed to produce
Type C medicated feed containing 0.0125% amprolium.
• Use 1000 pounds of 2.5% Type B per ton of feed to produce
Type C medicated feed containing 1.25% amprolium.

AMOUNT AND DIRECTIONS FOR USE:
Prevention: 227 mg amprolium /100 lb (5 mg/kg) body weight per day for 21 days during periods of exposure or when
experience indicates that coccidiosis is likely to be a hazard.
Treatment: 454 mg amprolium/100 lb (10 mg/kg) bodyweight per day for 5 days. Use on a herd basis only; when one
or more calves show signs of coccidiosis, it is likely that the rest of the group has been exposed and all
calves in the group should be treated.
*To aid in even distribution of CORID 25% in the finished feed, prepare a mixture of CORID 25% in a portion of complete feed
ingredient before mixing into the finished ration. Blend the mixture with the remainder of the finished feed and mix thoroughly.

The proper amount of amprolium supplement is mixed with the amount of ration consumed in one day. The tables below
give suggested examples for using Type C medicated feed.

Distributed by:
Huvepharma, lnc.
Peachtree City, GA 30269